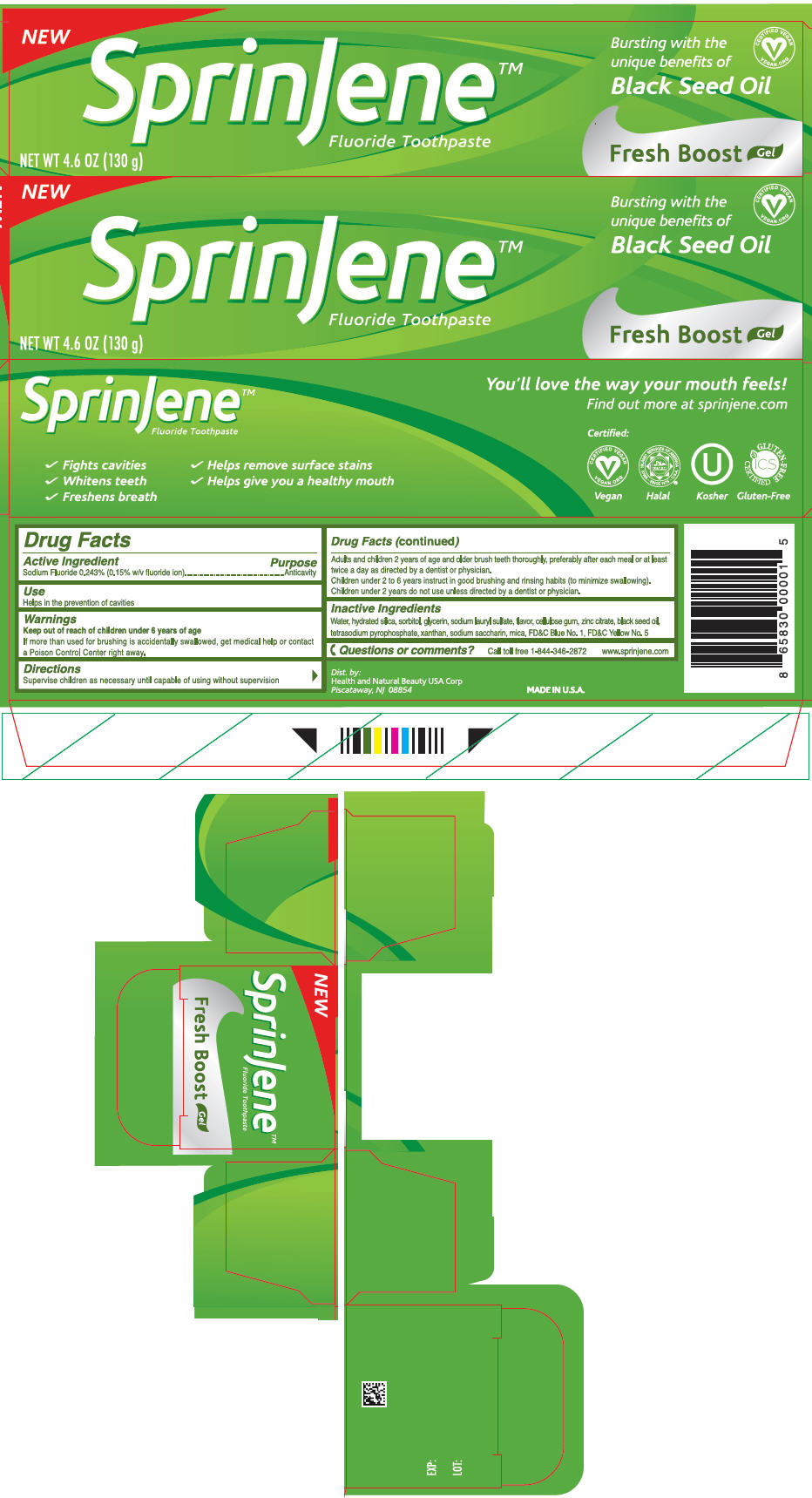 DRUG LABEL: SprinJene 
NDC: 63404-0910 | Form: GEL, DENTIFRICE
Manufacturer: Health and Natural Beauty USA Corp
Category: otc | Type: HUMAN OTC DRUG LABEL
Date: 20230202

ACTIVE INGREDIENTS: Sodium Fluoride 1.5 mg/1 g
INACTIVE INGREDIENTS: Water; Hydrated Silica; Glycerin; Sorbitol; Sodium Lauryl Sulfate; CARBOXYMETHYLCELLULOSE SODIUM, UNSPECIFIED; Zinc Citrate; Guizotia Abyssinica Seed Oil; Sodium Pyrophosphate; Xanthan Gum; Saccharin Sodium; Mica; FD&C Blue No. 1; FD&C Yellow No. 5

SprinJene™
Fresh Boost

Drug Facts

Active Ingredient

Sodium Fluoride 0.243% (0.15% w/v fluoride ion)

Purpose

Anticavity

Use

Helps in the prevention of caries

Warnings

Keep out of reach of children under 6 years of age

If more than used for brushing is accidentally swallowed, get medical help or contact a Poison Control Center right away.

Directions

Supervise children as necessary until capable of using without supervision

Adults and children 2 years of age and older brush teeth thoroughly, preferably after each meal or at least twice a day as directed by a dentist or physician.

Children under 2 to 6 years instruct in good brushing and rinsing habbits (to minimize swallowing).

Children under 2 years do not use unless directed by a dentist or physician.

Inactive Ingredients

Water, hydrated silica, sorbitol, glycerin, sodium lauryl sulfate, flavor, cellulose gum, tetrasodium pyrophosphate, zinc citrate, black seed oil, xanthan, sodium saccharin, mica, FD&C Blue No. 1, FD&C Yellow No. 5

Questions or comments?

Call toll free 1-844-3-462872
www.sprinjene.com

Dist. by:
Health and Natural Beauty USA Corp
Piscataway, NJ 08854

PRINCIPAL DISPLAY PANEL - 130 g Tube Carton

NEW

SprinJene™
Fluoride Toothpaste

Bursting with the
unique benefits of
Black Seed Oil

CERTIFIED VEGAN
VEGAN.ORG

Fresh Boost Gel

NET WT 4.6 OZ (130 g)